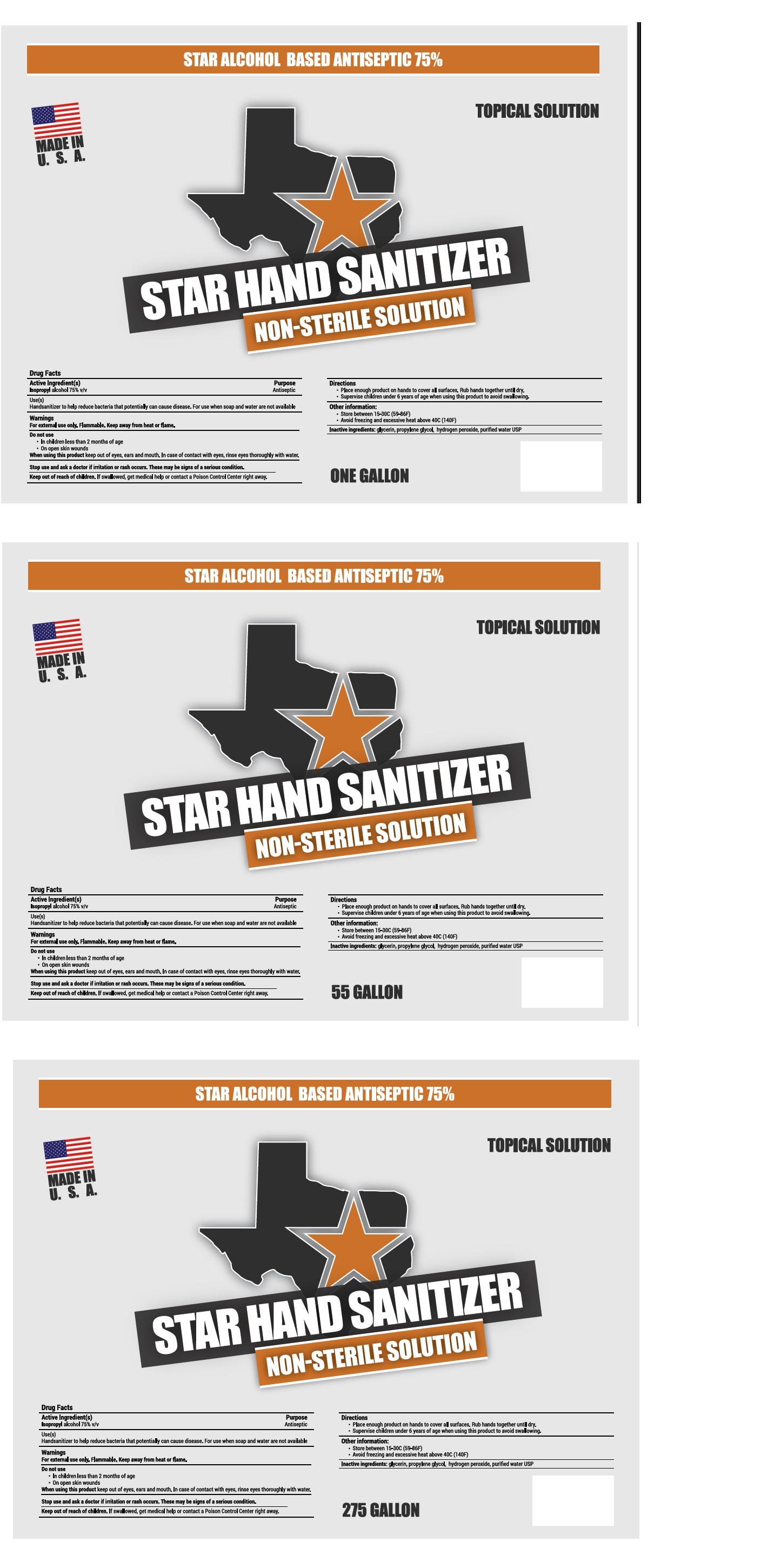 DRUG LABEL: STAR HAND SANITIZER
NDC: 74603-070 | Form: SOLUTION
Manufacturer: Sound Resource Solutions LLC
Category: otc | Type: HUMAN OTC DRUG LABEL
Date: 20200406

ACTIVE INGREDIENTS: ISOPROPYL ALCOHOL 75 L/100 L
INACTIVE INGREDIENTS: GLYCERIN; PROPYLENE GLYCOL; HYDROGEN PEROXIDE; WATER

STAR HAND SANITIZER

Active Ingredient(s)

Isopropyl alcohol 75% v/v

Purpose

Antiseptic

Use(s)

Hand sanitizer to help reduce bacteria that potentially can cause disease. For use when soap and water are not available

Warnings

For external use only. Flammable. Keep away from heat or flame.

Do not use

• In children less than 2 months of age

• On open skin wounds

When using this product keep out of eyes, ears and mouth. In case of contact with eyes, rinse eyes thoroughly with water.

Stop use and ask a doctor if irritation or rash occurs. These may be signs of a serious condition.

Keep out of reach of children. If swallowed, get medical help or contact a Poison Control Center right away.

Directions

• Place enough product on hands to cover all surfaces. Rub hands together until dry.

• Supervise children under 6 years of age when using this product to avoid swallowing.

Other information:

• Store between 15-30C (59-86F)

• Avoid freezing and excessive heat above 40C (140F)

Inactive ingredients:

glycerin, propylene glycol, hydrogen peroxide, purified water USP

STAR ALCOHOL BASED ANTISEPTIC 75%
MADE IN U.S.A.
NON-STERILE SOLUTION

TOPICAL SOLUTION